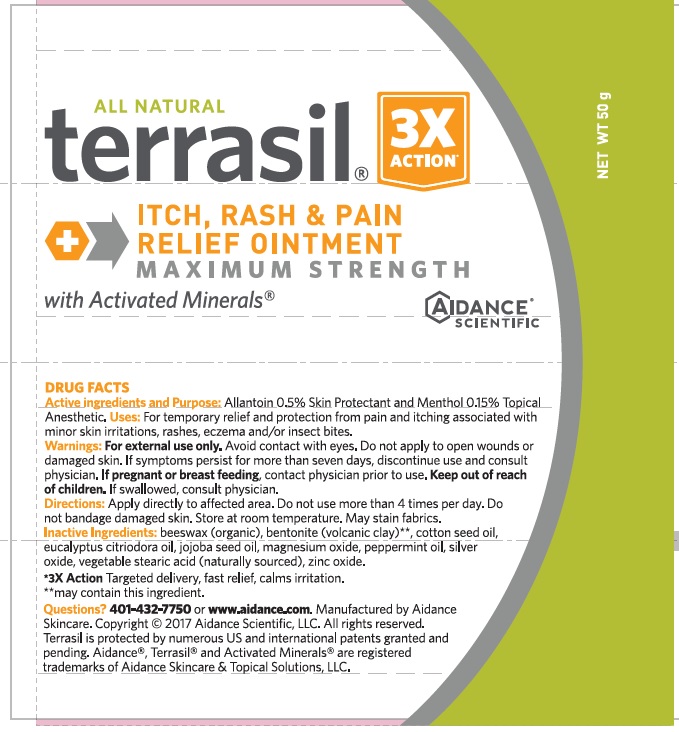 DRUG LABEL: Terrasil Itch, Rash and Pain Relief Maximum Strength
NDC: 24909-160 | Form: OINTMENT
Manufacturer: Aidance Skincare & Topical Solutions, LLC
Category: otc | Type: HUMAN OTC DRUG LABEL
Date: 20190104

ACTIVE INGREDIENTS: ALLANTOIN 0.5 1/100 g; MENTHOL 0.15 g/100 g
INACTIVE INGREDIENTS: BENTONITE; COTTONSEED OIL; EUCALYPTUS OIL; JOJOBA OIL; MAGNESIUM OXIDE; PEPPERMINT OIL; SILVER OXIDE; STEARIC ACID; WHITE WAX; ZINC OXIDE

Terrasil Itch, Rash and Pain Relief Maximum Strength

Active Ingredients

Allantoin 0.5%, Menthol 0.15%

Purpose

Allantoin - Skin Protectant
Menthol - Topical Anesthetic

Uses

For temporary relief and protection from pain and itching associated with minor skin irritations, rashes, eczema and/or insect bites.

Warnings

For external use only. Avoid contact with eyes. Do not apply to open wounds or damaged skin. If symptoms persist for more than seven days, discontinue use and consult physician. If pregnant or breast feeding, contact physician prior to use.

Keep out of reach of children. If swallowed, consult physician.

Directions

Apply directly to affected area. Do not use more than 4 times per day. Do not bandage damaged skin. Store at room temperature. May stain fabrics.

Inactive Ingredients

beeswax (organic), bentonite (volcanic clay)**, cotton seed oil, eucalyptus citriodora oil, jojoba seed oil, magnesium oxide, peppermint oil, silver oxide, vegetable stearic acid (naturally sourced), zinc oxide.

**may contain this ingredient.

PRINCIPAL DISPLAY PANEL

All Natural
terrasil®
ITCH, RASH & PAIN RELIEF OINTMENT
MAXIMUM STRENGTH
with Activated Minerals®